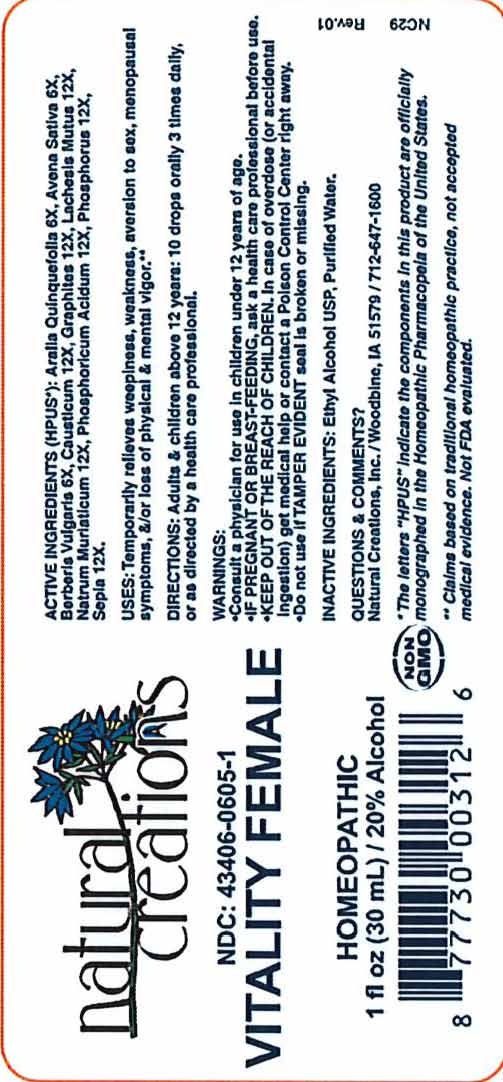 DRUG LABEL: Vitality Female
NDC: 43406-0605 | Form: LIQUID
Manufacturer: Natural Creations, Inc
Category: homeopathic | Type: HUMAN OTC DRUG LABEL
Date: 20181221

ACTIVE INGREDIENTS: AMERICAN GINSENG 6 [hp_X]/1 mL; AVENA SATIVA FLOWERING TOP 6 [hp_X]/1 mL; BERBERIS VULGARIS ROOT BARK 6 [hp_X]/1 mL; CAUSTICUM 12 [hp_X]/1 mL; GRAPHITE 12 [hp_X]/1 mL; LACHESIS MUTA VENOM 12 [hp_X]/1 mL; SODIUM CHLORIDE 12 [hp_X]/1 mL; PHOSPHORIC ACID 12 [hp_X]/1 mL; PHOSPHORUS 12 [hp_X]/1 mL; SEPIA OFFICINALIS JUICE 12 [hp_X]/1 mL
INACTIVE INGREDIENTS: ALCOHOL; WATER

Vitality Female

ACTIVE INGREDIENT

ACTIVE INGREDIENTS (*HPUS): Aralia Quinquefolia 6X, Avena Sativa 6X, Berberis Vulgaris 6X, Causticum 12X, Graphites 12X, Lachesis Mutus 12X, Natrum Muriaticum 12X, Phosphoricum Acidum 12X, Phosphorus 12X, Sepia 12X

INDICATIONS AND USAGE

USES: Temporarily relieves weepiness, weakness, aversion to sex, menopausal symptoms, &/or loss of physical & mental vigor.**

PURPOSE

USES: Temporarily relieves weepiness, weakness, aversion to sex, menopausal symptoms, &/or loss of physical & mental vigor.**

DOSAGE AND ADMINISTRATION

DIRECTIONS: Adults & children above 12 years: 10 drops orally 3 times daily, or as directed by a health care professional.

KEEP OUT OF REACH OF CHILDREN

KEEP OUT OF THE REACH OF CHILDREN. In case of overdose (or accidental ingestion) get medical help or contact a Poison Control Center right away.

WARNINGS:

- Consult a physician for use in children under 12 years of age.
- IF PREGNANT OR BREAST-FEEDING, ask a health care professional before use.
- KEEP OUT OF THE REACH OF CHILDREN. In case of overdose (or accidental ingestion) get medical help or contact a Poison Control Center right away.
- Do not use if TAMPER EVIDENT seal is broken or missing.

INACTIVE INGREDIENTS: Ethyl Alcohol USP, Purified Water.

QUESTIONS & COMMENTS?

Natural Creations, Inc. / Woodbine, IA 51579 / 712-647-1600

REFERENCES

*The letters "HPUS" indicate the components in this product are officially monographed in the Homeopathic Pharmacopeia of the United States.

**Claims based on traditional homeopathic practice, not accepted medical evidence. Not FDA evaluated.

PACKAGE LABEL

NDC:43406-0605-1

Vitality Female

HOMEOPATHIC

1 fl oz (30mL) / 20% Alcohol